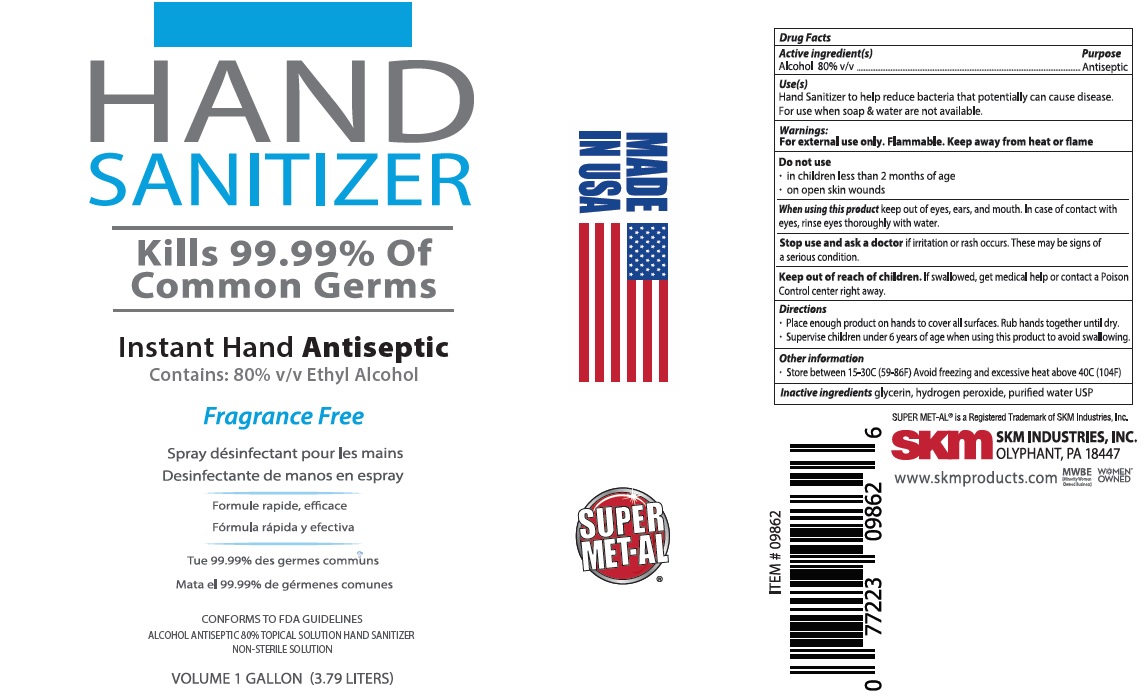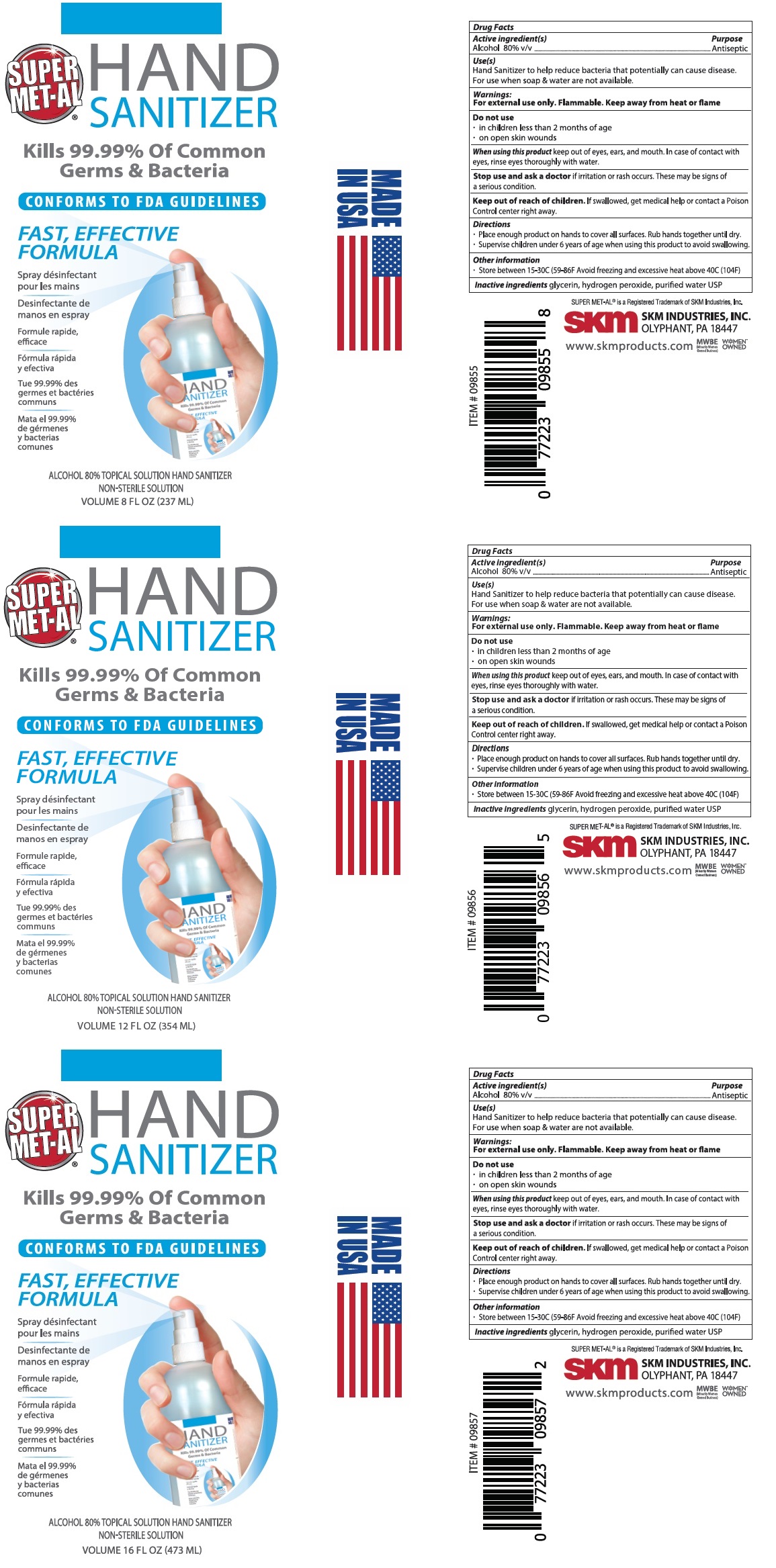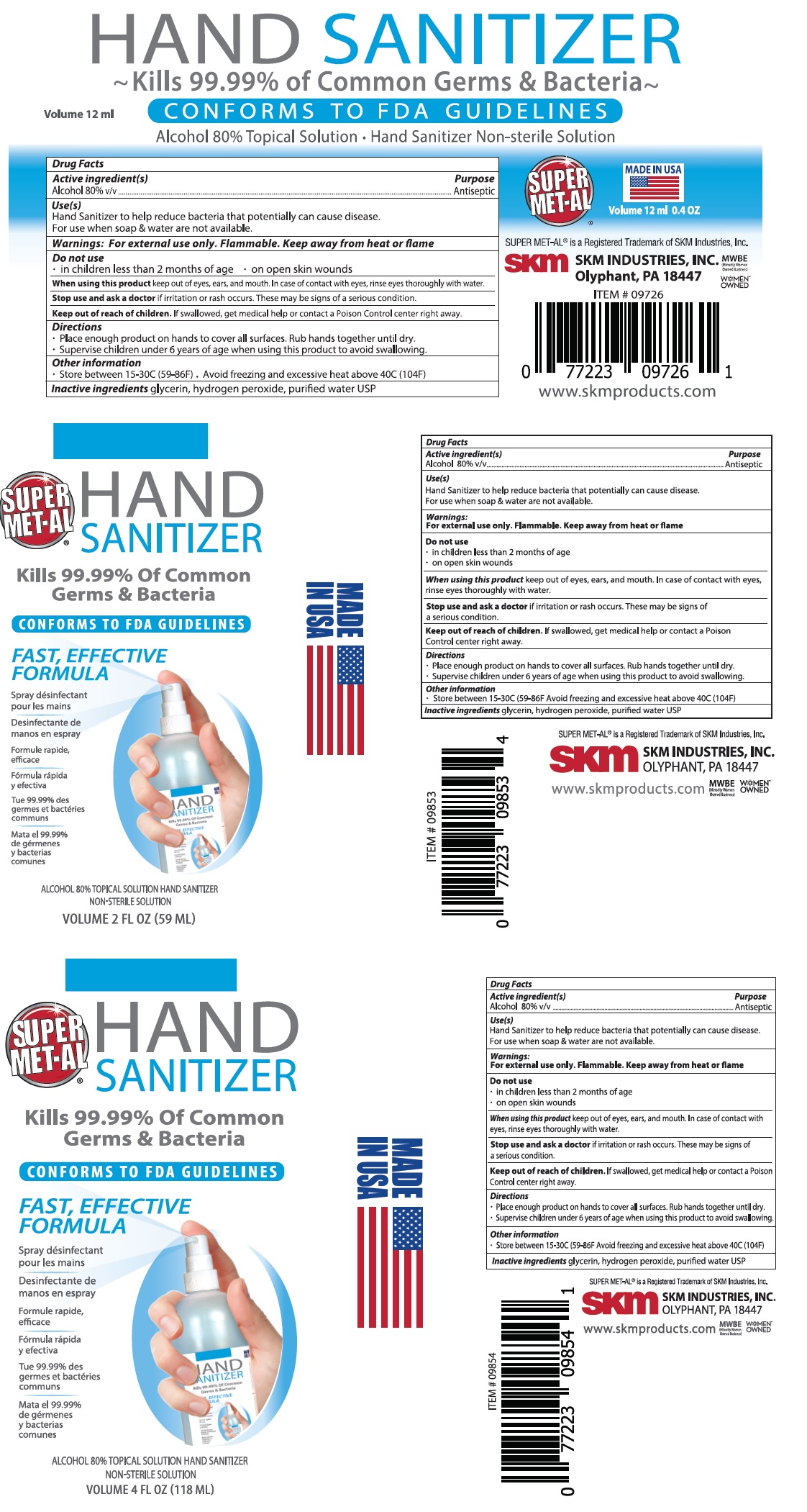 DRUG LABEL: SUPER MET-AL HAND SANITIZER
NDC: 74990-002 | Form: SPRAY
Manufacturer: Skm Industries Inc.
Category: otc | Type: HUMAN OTC DRUG LABEL
Date: 20200611

ACTIVE INGREDIENTS: ALCOHOL 80 mL/100 mL
INACTIVE INGREDIENTS: GLYCERIN; HYDROGEN PEROXIDE; WATER

SUPER MET-AL HAND SANITIZER

Active ingredient(s)

Alcohol 80% v/v

Purpose

Antiseptic

Use(s)

Hand Sanitizer to help reduce bacteria that potentially can cause disease.

For use when soap & water are not available.

Warnings:

For external use only. Flammable. Keep away from heat or flame

Do not use

• in children less than 2 months of age • on open skin wounds

When using this product keep out of eyes, ears and mouth. In case of contact with eyes, rinse eyes thoroughly with water.

Stop use and ask a doctor if irritation or rash occurs. These may be signs of a serious condition.

Keep out of reach of children. If swallowed, get medical help or contact a Poison Control Center right away.

Directions

• Place enough product on hands to cover all surfaces. Rub hands together until dry.

• Supervise children under 6 years of age when using this product to avoid swallowing.

Other information

• Store between 15-30°C (59-86°F) • Avoid freezing and excessive heat above 40°C (104°F)

Inactive ingredients glycerin, hydrogen peroxide, purified water USP

Kills 99.99% of Common Germs & Bacteria

CONFORMS TO FDA GUIDELINES

FAST, EFFECTIVE FORMULA

ALCOHOL 80% TOPICAL SOLUTION HAND SANITIZER

NON-STERILE SOLUTION

MADE IN USA

SUPER MET-AL® is a Registered Trademark of SKM Industries, Inc.

SKM INDUSTRIES INC.

Olyphant, PA 18447

www.skmproducts.com